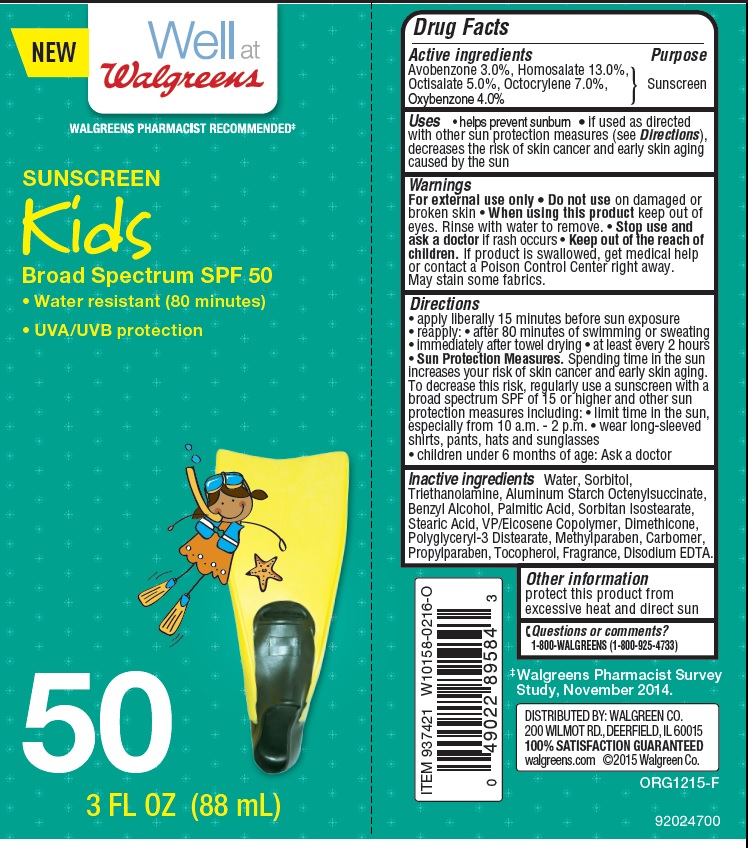 DRUG LABEL: WALGREENS KIDS SPF 50 
NDC: 0363-4018 | Form: LOTION
Manufacturer: Walgreens
Category: otc | Type: HUMAN OTC DRUG LABEL
Date: 20160308

ACTIVE INGREDIENTS: AVOBENZONE 3 g/100 g; HOMOSALATE 13 g/100 g; OCTISALATE 5 g/100 g; OCTOCRYLENE 7 g/100 g; OXYBENZONE 4 g/100 g
INACTIVE INGREDIENTS: WATER; SORBITOL; TROLAMINE; ALUMINUM STARCH OCTENYLSUCCINATE; BENZYL ALCOHOL; PALMITIC ACID; SORBITAN ISOSTEARATE; STEARIC ACID; DIMETHICONE; POLYGLYCERYL-3 DISTEARATE; CARBOXYPOLYMETHYLENE; TOCOPHEROL; EDETATE DISODIUM; METHYLPARABEN; PROPYLPARABEN

Drug Facts

Active ingredients

Avobenzone 3.0%, Homosalate 13.0%, Octisalate 5.0%, Octocrylene 7.0%, Oxybenzone 4.0%

Purpose

Sunscreen

Uses

- helps prevent sunburn
- if used as directed with other sun protection measures (see Directions), decreases the risk of skin cancer and early skin aging caused by the sun

Warnings

For external use only

Do not use

on damaged or broken skin

When using this product

keep out of eyes. Rinse with water to remove.

Stop use and ask a doctor

if rash occurs

Keep out of reach of children

If product is swallowed, get medical help or contact a Poison Control Center right away.

- May stain some fabrics

Directions

- apply liberally 15 minutes before sun exposure
- reapply: after 80 minutes of swimming or sweating
- immediately after towel drying
- at least every 2 hours
  Sun Protection Measures. Spending time in the sun increases your risk of skin cancer and early skin aging. To decrease this risk, regularly use a sunscreen with broad spectrum SPF of 15 or higher and other sun protection measures including:
- limit time in sun, especially from 10.00 a.m. - 2.00 p.m.
- wear long-sleeve shirts, pants, hats and sunglasses
- children under 6 months of age: Ask a doctor

Inactive ingredients

Water, Sorbitol, Triethanolamine, Aluminum Starch Octenylsuccinate, Benzyl Alcohol, Palmitic Acid, Sorbitan Isostearate, Stearic Acid, VP/Eicosene Copolymer, Dimethicone, Polyglyceryl-3 Distearate, Carbomer, Tocopherol, Disodium EDTA, Methylparaben, Propylparaben.

Other information

protect this product from excessive heat and direct sun

Questions or Comments

1-800-WALGREENS (1-800-925-4733)

Principal Display Panel

NDC - 0360-4018-22

NEW Well at Walgreens

WALGREENS PHARMACIST RECOMMENDED*

SUNSCREEN

Kids

Broad Spectrum SPF 50

- Water-resistant (80 minutes)
- UVA/UVB protection

50

3 FL OZ (88 mL)